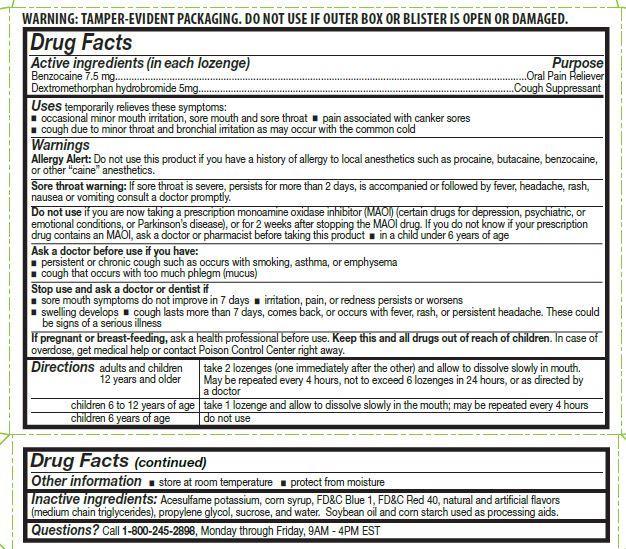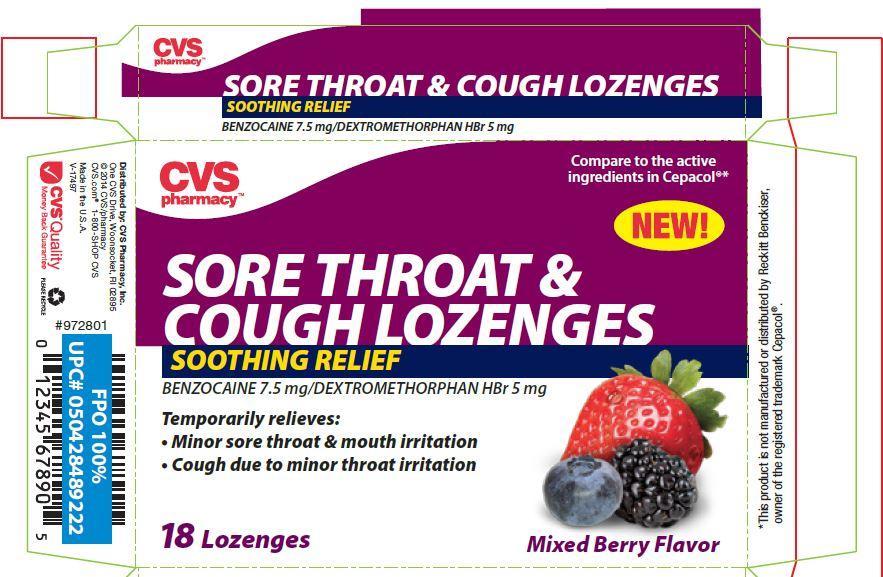 DRUG LABEL: CVS Sore Throat Mixed Berry Flavor
NDC: 59779-649 | Form: LOZENGE
Manufacturer: CVS Pharmacy, Inc.
Category: otc | Type: HUMAN OTC DRUG LABEL
Date: 20140422

ACTIVE INGREDIENTS: BENZOCAINE 7.5 mg/1 1; DEXTROMETHORPHAN HYDROBROMIDE 5 mg/1 1
INACTIVE INGREDIENTS: ACESULFAME POTASSIUM; FD&C BLUE NO. 1; FD&C RED NO. 40; CORN SYRUP; PROPYLENE GLYCOL; SUCROSE; WATER; SOYBEAN OIL; STARCH, CORN

CVS Mixed Berry Sore Throat

ACTIVE INGREDIENT

Active ingredients (in each lozenge) | Purpose
Benzocaine 7.5 mg | Oral Pain Reliever
Dextromethorphan hydrobromide 5 mg | Oral Pain Reliever

Uses

temporarily relieves these symptoms:

- occasional minor irritation, pain, sore mouth and sore throat
- pain associated with canker sores
- cough due to minor throat and bronchial irritation as may occur with common cold

Warnings

Allergy Alert: Do not use this product if you have a history of allergy to local anesthetics such as procaine, butacaine, benzocaine, or any other "caine" anesthetics.

Sore throat warning:

Severe or persistent sore throat or sore throat accompanied by high fever, headache, rash, nausea, and vomiting may be serious. Consult a dentist or doctor right away. Do not use more than 2 days or administer to children under 5 years of age unless directed by a doctor.

Do not use if you are now taking a prescription monoamine oxidase inhibitor (MAOI) (certain drugs for depression, psychiatric, or emotional conditions, or Parkinson’s disease), or for 2 weeks after stopping the MAOI drug. If you do not know if your prescription drug contains an MAOI, ask a doctor or pharmacist before taking this product.

Ask a doctor before use if you have:

• persistent or chronic cough such as occurs with smoking, asthma, chronic bronchitis or emphysema

• cough that occurs with too much phlegm (mucus)

Stop Use and ask a doctor or dentist if

- sore mouth symptom do not improve in 7 days
- irritation, pain or redness persists or worsens
- swelling developes
- cough lasts for more than 7 days, comes back, or is accompanied by fever, rash, or persistent headache. A persistent cough may be a sign of a serious condition.

PREGNANCY OR BREAST FEEDING

If pregnant or breast-feeding, ask a health professional before use.

KEEP OUT OF REACH OF CHILDREN

Keep this and all drugs out of the reach of children.

In case of overdose, get medical help or contact a Poison Control Center right away.

Directions

- adults and children 12 years and older: take 2 lozenges (one immediately after the other) and allow to dissolve slowly in the mouth. May be repeated every 4 hours, not to exceed 6 lozenges in 24-hours, or as directed by a doctor

- children 6 to under 12 years of age: take 1 lozenge and allow to dissolve slowly in the mouth; may be repeated every 4 hours

- children 6 years of age: do not use

Other information

- store at room temperature
- protect from moisture

Inactive ingredients

Acesulfame potassium, corn syrup, FD&C Blue #1, FD&C Red #40, natural and artificial flavors (medium chain triglycerides), propylene glycol, sucrose, and water. Soybean oil and corn starch used as processing aids.

Questions ?

Call 1-800-245-2898. Monday through Friday, 9AM - 4PM EST.

CVS Sore Throat Lozenges Mixed Berry Flavor 18 Count (59779-649-18)

CVS pharmacy

compare to the active ingredients in Cepacol**

SORE THROAT &

COUGH LOZENGES

SOOTHING RELIEF

BENZOCAINE 7.5 mg/DEXTROMETHORPHAN HBr 5 mg

Temporarily relieves:

- Minor sore throat &mouth irritation
- Cough due to minor throat irritation

Mixed Berry Flavor

18 LOZENGES

DISTRIBUTED BY:

CVS Pharmacy, Inc.

One Cvs Drive Woonsocket, RI 02895

2014 CVS/Pharmacy

CVS.com 1-800-SHOP CVS

Made in the USA

This product is not manufactured or distributed

by Reckftt Bencldser owner af the registered

trademark Cepacol.